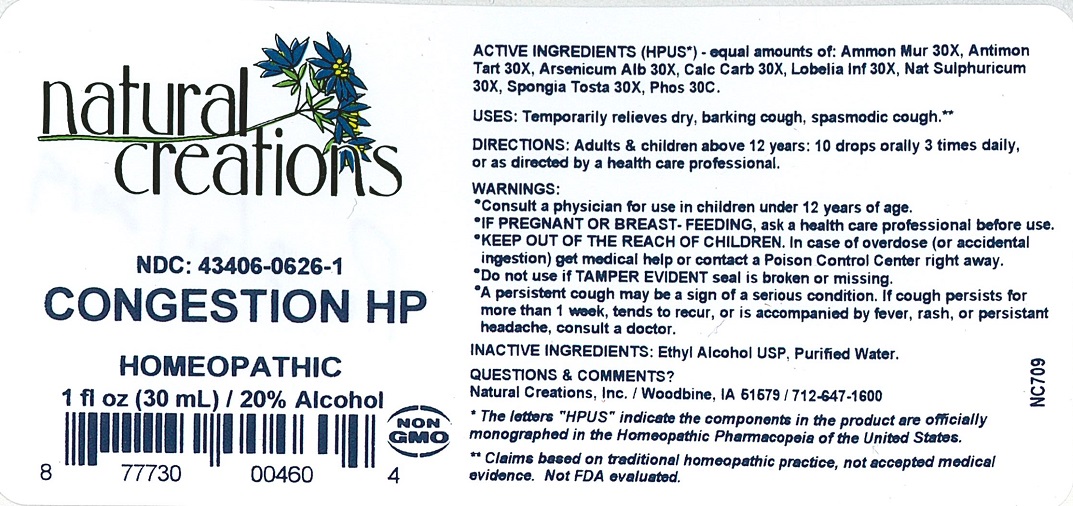 DRUG LABEL: CONGESTION HP
NDC: 43406-0626 | Form: LIQUID
Manufacturer: Natural Creations, Inc.
Category: homeopathic | Type: HUMAN OTC DRUG LABEL
Date: 20251120

ACTIVE INGREDIENTS: AMMONIUM CHLORIDE 30 [hp_X]/1 mL; ANTIMONY POTASSIUM TARTRATE 30 [hp_X]/1 mL; ARSENIC TRIOXIDE 30 [hp_X]/1 mL; OYSTER SHELL CALCIUM CARBONATE, CRUDE 30 [hp_X]/1 mL; LOBELIA INFLATA 30 [hp_X]/1 mL; SODIUM SULFATE 30 [hp_X]/1 mL; SPONGIA OFFICINALIS SKELETON, ROASTED 30 [hp_X]/1 mL; PHOSPHORUS 30 [hp_C]/1 mL
INACTIVE INGREDIENTS: WATER; ALCOHOL

CONGESTION HP

ACTIVE INGREDIENT

ACTIVE INGREDIENTS (HPUS*)- equal amounts of: Ammon Mur 30X, Antimon Tart 30X, Arsenicum Alb 30X, Calc Carb 30C, Lobelia Inf 30X, Nat Sulphuricum 30X, Spongia Tosta 30X, Phos 30C

PURPOSE

USES: Temporarily relieves dry, barking cough, spasmodic cough.**

INDICATIONS AND USAGE

USES: Temporarily relieves dry, barking cough, spasmodic cough.**

DOSAGE AND ADMINISTRATION

Directions: Adults & children above 12 years: 10 drops orally 3 times daily, or as directed by a health care professional.

KEEP OUT OF REACH OF CHILDREN

KEEP OUT OF THE REACH OF CHILDREN. In case of overdose (or accidental ingestion) get medical help or contact a Poison Control Center right away.

WARNINGS:

- Consult a physician for use in children under 12 years of age.
- IF PREGNANT OR BREAST-FEEDING, ask a health care professional before use.
- KEEP OUT OF THE REACH OF CHILDREN. In case of overdose (or accidental ingestion) get medical help or contact a Poison Control Center right away.
- Do not use if TAMPER EVIDENT seal is broken or missing.
- A persistent cough may be a sign of a serious condition. If cough persists for more than 1 week, tends to recur, or is accompanied by fever, rash, or persistent headache consult a doctor.

Inactive Ingredients: Ethyl Alcohol USP, Purified Water.

QUESTIONS & COMMENTS?

Natural Creations, Inc. / Woodbine, IA 51579 / 712-647-1600

REFERENCES

*The letters “HPUS” indicate the components in the product are officially monographed in the Homeopathic Pharmacopeia of the United States.

**Claims based on traditional homeopathic practice, not accepted medical evidence. Not FDA evaluated.

PACKAGE LABEL

NDC: 43406-0626-1

CONGESTION HP

HOMEOPATHIC

1 fl oz (30 mL) 20% Alcohol

877730004604